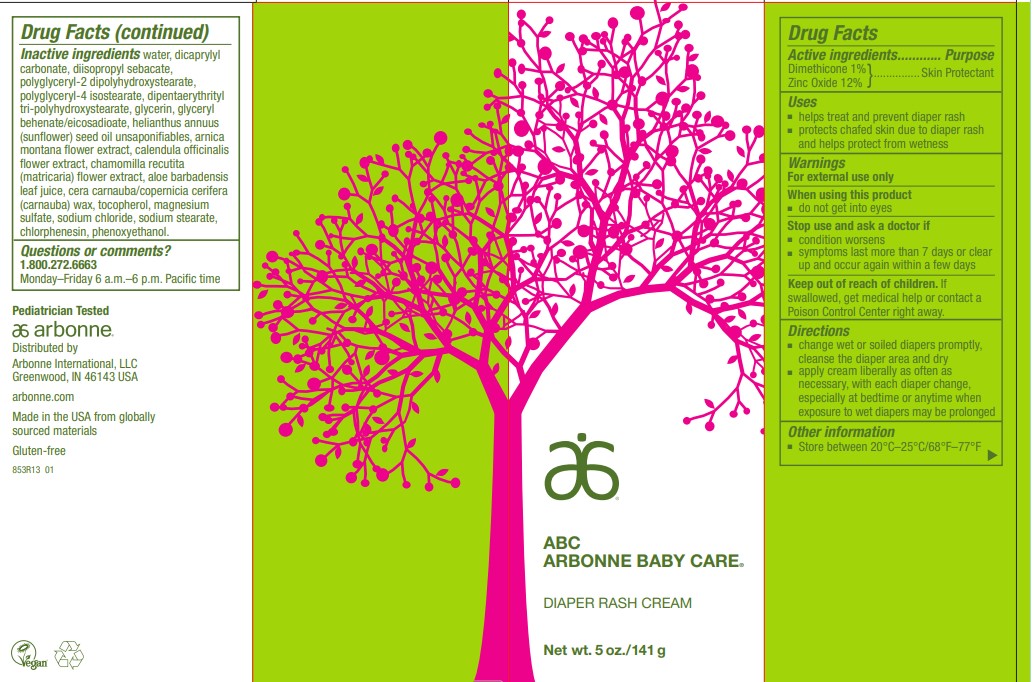 DRUG LABEL: ABC Arbonne Baby Care Diaper Rash
NDC: 42508-331 | Form: CREAM
Manufacturer: Arbonne International, LLC
Category: otc | Type: HUMAN OTC DRUG LABEL
Date: 20241108

ACTIVE INGREDIENTS: DIMETHICONE 10 mg/1 g; ZINC OXIDE 120 mg/1 g
INACTIVE INGREDIENTS: ALOE VERA LEAF; ARNICA MONTANA FLOWER; CALENDULA OFFICINALIS FLOWER; CHAMOMILE; CHLORPHENESIN; CARNAUBA WAX; DICAPRYLYL CARBONATE; DIISOPROPYL SEBACATE; DIPENTAERYTHRITYL TRI-POLYHYDROXYSTEARATE; GLYCERIN; GLYCERYL BEHENATE/EICOSADIOATE; SUNFLOWER OIL UNSAPONIFIABLES; MAGNESIUM SULFATE ANHYDROUS; PHENOXYETHANOL; POLYGLYCERYL-2 DIPOLYHYDROXYSTEARATE; POLYGLYCERYL-4 ISOSTEARATE; SODIUM CHLORIDE; SODIUM STEARATE; .ALPHA.-TOCOPHEROL, DL-; WATER

ABC Arbonne Baby Care®Diaper Rash

Drug Facts

Active ingredients

Dimethicone 1%
Zinc Oxide 12%

Purpose

Skin Protectant

Uses

- helps treat and prevent diaper rash
- protects chafed skin due to diaper rash and helps protect from wetness

Warnings

For external use only

When using this product

- do not get into eyes

Stop use and ask a doctor if

- condition worsens
- symptoms last more than 7 days or clear up and occur again within a few days

Keep out of reach of children.If swallowed, get medical help or contact a Poison Control Center right away.

Directions

- change wet or soiled diapers promptly, cleanse the diaper area and dry
- apply cream liberally as often as necessary, with each diaper change, especially at bedtime or anytime when exposure to wet diapers may be prolonged

Other information

- Store between 20°C–25°C/68°F–77°F

Inactive ingredients

water, dicaprylyl carbonate, diisopropyl sebacate, polyglyceryl-2 dipolyhydroxystearate, polyglyceryl-4 isostearate, dipentaerythrityl tri-polyhydroxystearate, glycerin, glyceryl behenate/eicosadioate, helianthus annuus (sunflower) seed oil unsaponifiables, arnica montana flower extract, calendula officinalis flower extract, chamomilla recutita (matricaria) flower extract, aloe barbadensis leaf juice, cera carnauba/copernicia cerifera (carnauba) wax, tocopherol, magnesium sulfate, sodium chloride, sodium stearate, chlorphenesin, phenoxyethanol.

Questions or comments?

1.800.272.6663

Monday–Friday 6 a.m.–6 p.m. Pacific time

Distributed by
Arbonne International, LLC
Greenwood, IN 46143 USA

PRINCIPAL DISPLAY PANEL - 141 g Tube Carton

ABC
ARBONNE BABY CARE®

DIAPER RASH CREAM

Net wt. 5 oz./141 g